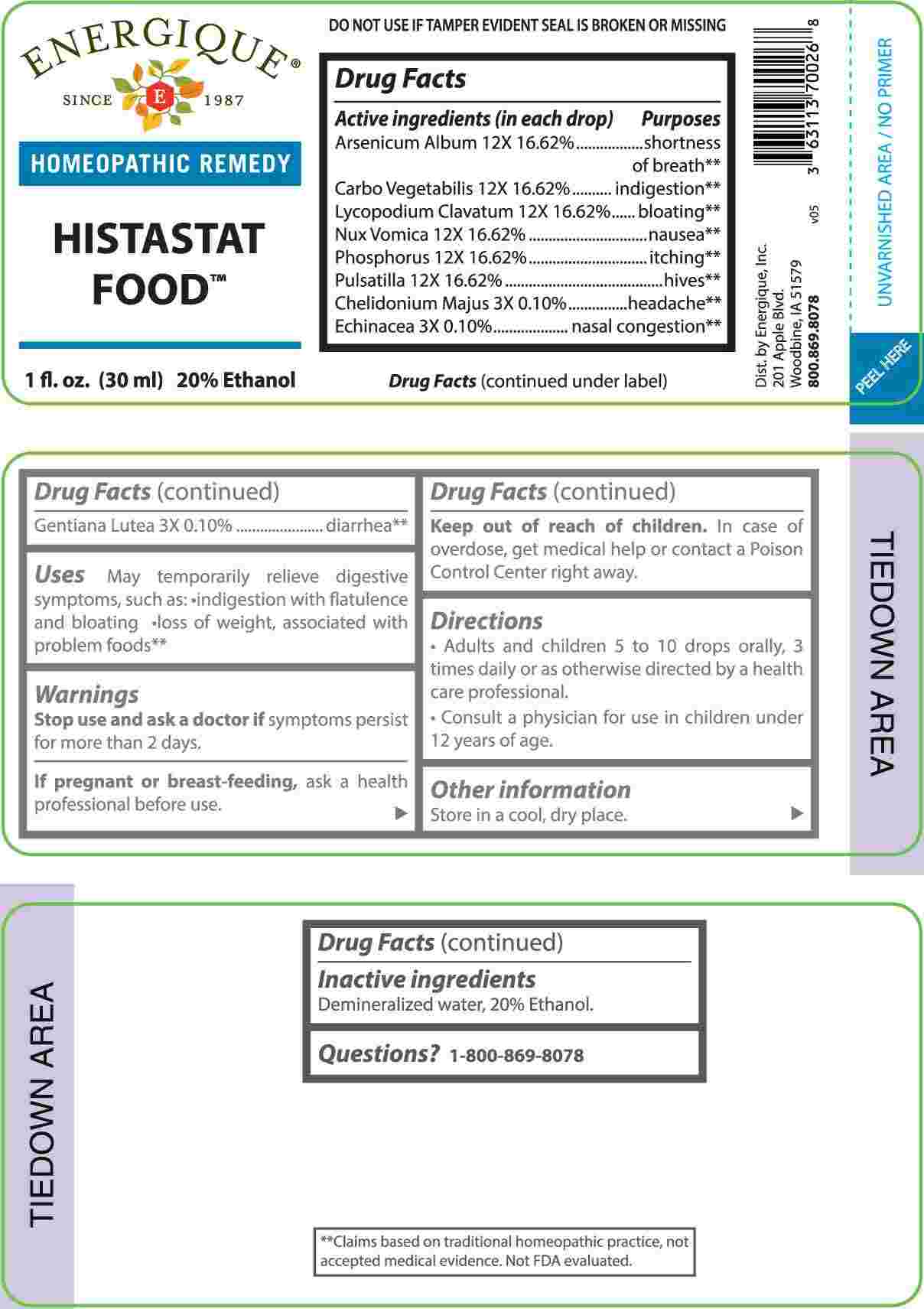 DRUG LABEL: Histastat Food
NDC: 44911-0574 | Form: LIQUID
Manufacturer: Energique, Inc.
Category: homeopathic | Type: HUMAN OTC DRUG LABEL
Date: 20240726

ACTIVE INGREDIENTS: CHELIDONIUM MAJUS WHOLE 3 [hp_X]/1 mL; ECHINACEA ANGUSTIFOLIA WHOLE 3 [hp_X]/1 mL; GENTIANA LUTEA ROOT 3 [hp_X]/1 mL; ARSENIC TRIOXIDE 12 [hp_X]/1 mL; ACTIVATED CHARCOAL 12 [hp_X]/1 mL; LYCOPODIUM CLAVATUM SPORE 12 [hp_X]/1 mL; STRYCHNOS NUX-VOMICA SEED 12 [hp_X]/1 mL; PHOSPHORUS 12 [hp_X]/1 mL; PULSATILLA PRATENSIS WHOLE 12 [hp_X]/1 mL
INACTIVE INGREDIENTS: WATER; ALCOHOL

DRUG FACTS:

ACTIVE INGREDIENTS:

(in each drop) Arsenicum Album 12X 16.62%, Carbo Vegetabilis 12X 16.62%, Lycopodium Clavatum 12X 16.62%, Nux Vomica 12X 16.62%, Phosphorus 12X 16.62%, Pulsatilla 12X 16.62%, Chelidonium Majus 3X 0.10%, Echinacea 3X 0.10%, Gentiana Lutea 3X 0.10%.

PURPOSE:

Arsenicum Album – shortness of breath,** Carbo Vegetabilis - indigestion,** Lycopodium Clavatum - bloating,** Nux Vomica - nausea,** Phosphorus - itching,** Pulsatilla - hives,** Chelidonium Majus - headache,** Echinacea – nasal congestion,** Gentiana Lutea – diarrhea**

**Claims based on traditional homeopathic practice, not accepted medical evidence. Not FDA evaluated.

USES:

May temporarily relieve digestive symptoms, such as:

• indigestion with flatulence and bloating • loss of weight, associated with problem foods.**

**Claims based on traditional homeopathic practice, not accepted medical evidence. Not FDA evaluated.

WARNINGS:

Stop use and ask a doctor if symptoms persist for more than 2 days.

If pregnant or breastfeeding, ask a health professional before use.

Keep out of reach of children. In case of overdose, get medical help or contact a Poison Control Center right away.

DO NOT USE IF TAMPER EVIDENT SEAL IS BROKEN OR MISSING

Store in a cool, dry place.

KEEP OUT OF REACH OF CHILDREN:

In case of overdose, get medical help or contact a Poison Control Center right away.

DIRECTIONS:

• Adults and children 5 to 10 drops orally, 3 times daily or as otherwise directed by a health care professional.

• Consult a physician for use in children under 12 years of age.

INACTIVE INGREDIENTS:

Demineralized water, 20% Ethanol.

QUESTIONS:

Dist. by Energique, Inc.

201 Apple Blvd.

Woodbine, IA 51579

800.869.8078

PACKAGE LABEL DISPLAY:

ENERGIQUE
SINCE 1987
HOMEOPATHIC REMEDY
HISTASTAT FOOD
1 fl. oz. (30 ml)